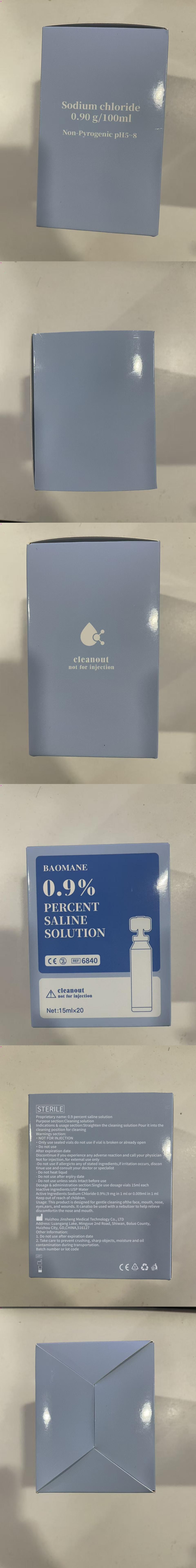 DRUG LABEL: 0.9 percentsaline
NDC: 87311-101 | Form: SOLUTION
Manufacturer: Huizhou Jinsheng Medical Technology Co., Ltd
Category: otc | Type: HUMAN OTC DRUG LABEL
Date: 20260203

ACTIVE INGREDIENTS: SODIUM CHLORIDE 9 mg/1 mL
INACTIVE INGREDIENTS: WATER

0.9 percent saline

PURPOSE

Cleaning solution

Keep out of reach of children

INDICATIONS AND USAGE

Straighten the cleaning solution Pour it into the cleaning position for cleaning

Usage: This product is designed for gentle cleaning of the face, mouth, nose, eyes,ears, and wounds. It can also be used with a nebulizer to help relieve discomfort in the nose and mouth.

WARNINGS

NOT FOR INJECTION

Only use sealed vials do not use if vial is broken or already open

Do not use After expiration date

Discontinue if you experience any adverse reaction and call your physician

Not for injection, for extemal use only

Do not use if allergicto any of stated Ingredients,if irritation occurs, discon tinue use and consult your doctor or speclalist

Do not heat liqud

Do not use after erplry date

Do not use unless seals Intact before use

Single use dosage vials 15ml each

Active ingredient: Sodium Chloride 0.9%

Inactive ingredient: USP Water

Other Information:
1. Do not use after expiration date
2. Take care to prevent crushing, sharp objects, moisture and oil contamination during transportation.

QUESTIONS

Manufacturer:

Huizhou Jinsheng Medical Technology Co., Ltd

Luangang Dahu, Shiwan Mingyue 2nd Road, Boluo County, Huizhou, Guangdong, China, 516000

See Label